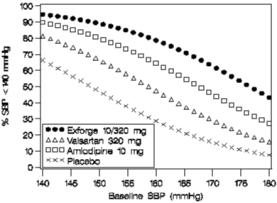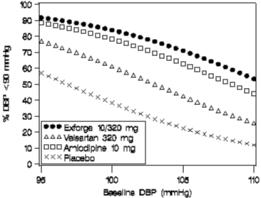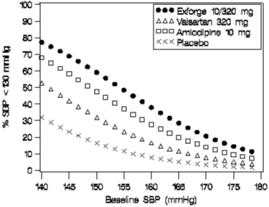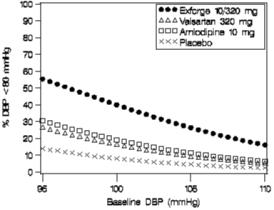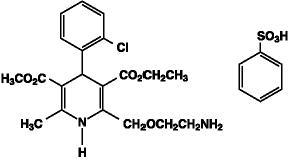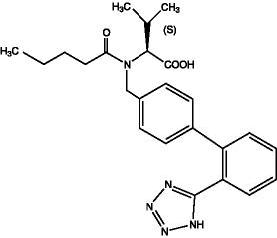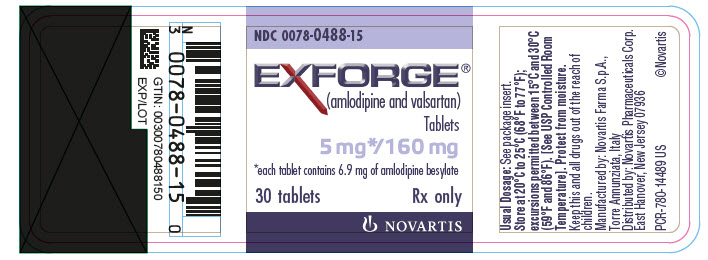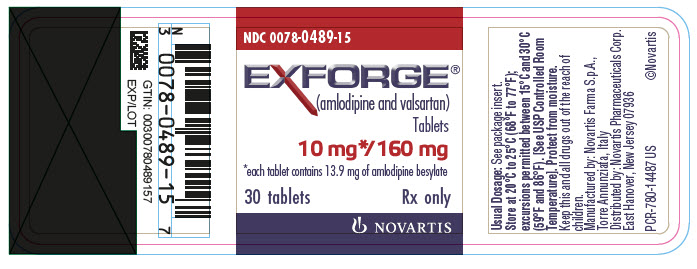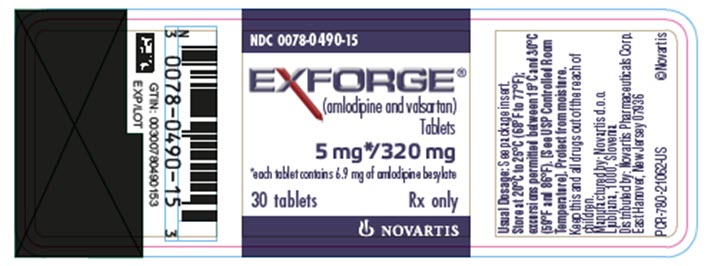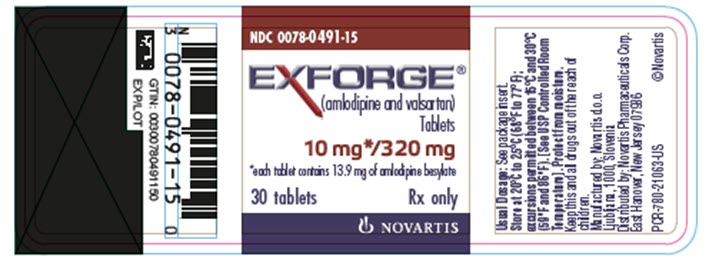 DRUG LABEL: Exforge
NDC: 0078-0488 | Form: TABLET, FILM COATED
Manufacturer: Novartis Pharmaceuticals Corporation
Category: prescription | Type: HUMAN PRESCRIPTION DRUG LABEL
Date: 20260217

ACTIVE INGREDIENTS: AMLODIPINE BESYLATE 5 mg/1 1; VALSARTAN 160 mg/1 1
INACTIVE INGREDIENTS: SILICON DIOXIDE; CROSPOVIDONE; HYPROMELLOSES; FERRIC OXIDE YELLOW; MAGNESIUM STEARATE; CELLULOSE, MICROCRYSTALLINE; POLYETHYLENE GLYCOL; TALC; TITANIUM DIOXIDE

HIGHLIGHTS OF PRESCRIBING INFORMATION

These highlights do not include all the information needed to use EXFORGE safely and effectively. See full prescribing information for EXFORGE.
EXFORGE® (amlodipine and valsartan) tablets, for oral use
Initial U.S. Approval: 2007

WARNING: FETAL TOXICITY

See full prescribing information for complete boxed warning.

- When pregnancy is detected, discontinue Exforge as soon as possible. (5.1)
- Drugs that act directly on the renin-angiotensin system can cause injury and death to the developing fetus. (5.1)

1 INDICATIONS AND USAGE

Exforge is the combination tablet of amlodipine, a dihydropyridine calcium channel blocker (DHP CCB), and valsartan, an angiotensin II receptor blocker (ARB). Exforge is indicated for the treatment of hypertension, to lower blood pressure:

- In patients not adequately controlled on monotherapy (1)
- As initial therapy in patients likely to need multiple drugs to achieve their blood pressure goals (1)

Lowering blood pressure reduces the risk of fatal and nonfatal cardiovascular events, primarily strokes and myocardial infarctions.

2 DOSAGE AND ADMINISTRATION

General Considerations:

- Majority of effect attained within 2 weeks (2.1)
- May be administered with other antihypertensive agents (2.1)

Hypertension:

- May be used as add-on therapy for patients not controlled on monotherapy (2.2)
- Patients who experience dose-limiting adverse reactions on monotherapy may be switched to Exforge containing a lower dose of that component (2.2)
- May be substituted for titrated components (2.3)
- When used as initial therapy: Initiate with 5/160 mg, then titrate upwards as necessary to a maximum of 10/320 mg once daily (2.4)

3 DOSAGE FORMS AND STRENGTHS

Tablets (amlodipine/valsartan mg): 5/160, 10/160, 5/320, 10/320 (3)

4 CONTRAINDICATIONS

Known hypersensitivity to any component;

Do not coadminister aliskiren with Exforge in patients with diabetes (4)

5 WARNINGS AND PRECAUTIONS

- Hypotension: Correct volume depletion prior to initiation (5.2)
- Increased angina and/or myocardial infarction (5.3)
- Monitor renal function and potassium in susceptible patients (5.4, 5.5)

6 ADVERSE REACTIONS

In placebo-controlled clinical trials, discontinuation due to side effects occurred in 1.8% of patients in the Exforge-treated patients and 2.1% in the placebo-treated group. The most common reasons for discontinuation of therapy with Exforge were peripheral edema and vertigo. The adverse experiences that occurred in clinical trials (≥ 2% of patients) at a higher incidence than placebo included peripheral edema, nasopharyngitis, upper respiratory tract infection, and dizziness. (6.1)

To report SUSPECTED ADVERSE REACTIONS, contact Novartis Pharmaceuticals Corporation at 1-888-669-6682 or FDA at 1-800-FDA-1088 or www.fda.gov/medwatch.

7 DRUG INTERACTIONS

- If simvastatin is coadministered with amlodipine, do not exceed doses greater than 20 mg daily of simvastatin (7)
- Non-Steroidal Anti-Inflammatory Drug (NSAID) use may lead to increased risk of renal impairment and loss of anti-hypertensive effect (7)
- Dual inhibition of the renin-angiotensin system: Increased risk of renal impairment, hypotension, and hyperkalemia (7)
- Lithium: Increases in serum lithium level and lithium toxicity (7)

8 USE IN SPECIFIC POPULATIONS

Lactation: Breastfeeding is not recommended (8.2)

Geriatric Patients: Not recommended for initial therapy (8.5)

Hepatic Impairment: Not recommended for initial therapy (8.7)

FULL PRESCRIBING INFORMATION

WARNING: FETAL TOXICITY

- When pregnancy is detected, discontinue Exforge as soon as possible. (5.1)
- Drugs that act directly on the renin-angiotensin system can cause injury and death to the developing fetus. (5.1)

1 INDICATIONS AND USAGE

1.1 Hypertension

Exforge (amlodipine and valsartan) is indicated for the treatment of hypertension, to lower blood pressure. Lowering blood pressure reduces the risk of fatal and nonfatal cardiovascular events, primarily strokes and myocardial infarctions. These benefits have been seen in controlled trials of antihypertensive drugs from a wide variety of pharmacologic classes, including amlodipine and the angiotensin II receptor blocker (ARB) class to which valsartan principally belongs. There are no controlled trials demonstrating risk reduction with Exforge.

Control of high blood pressure should be part of comprehensive cardiovascular risk management, including, as appropriate, lipid control, diabetes management, antithrombotic therapy, smoking cessation, exercise, and limited sodium intake. Many patients will require more than 1 drug to achieve blood pressure goals. For specific advice on goals and management, see published guidelines, such as those of the National High Blood Pressure Education Program’s Joint National Committee on Prevention, Detection, Evaluation, and Treatment of High Blood Pressure (JNC).

Numerous antihypertensive drugs, from a variety of pharmacologic classes and with different mechanisms of action, have been shown in randomized controlled trials to reduce cardiovascular morbidity and mortality, and it can be concluded that it is blood pressure reduction, and not some other pharmacologic property of the drugs, that is largely responsible for those benefits. The largest and most consistent cardiovascular outcome benefit has been a reduction in the risk of stroke, but reductions in myocardial infarction and cardiovascular mortality also have been seen regularly.

Elevated systolic or diastolic pressure causes increased cardiovascular risk, and the absolute risk increase per mmHg is greater at higher blood pressures, so that even modest reductions of severe hypertension can provide substantial benefit. Relative risk reduction from blood pressure reduction is similar across populations with varying absolute risk, so the absolute benefit is greater in patients who are at higher risk independent of their hypertension (for example, patients with diabetes or hyperlipidemia), and such patients would be expected to benefit from more aggressive treatment to a lower blood pressure goal.

Some antihypertensive drugs have smaller blood pressure effects (as monotherapy) in black patients, and many antihypertensive drugs have additional approved indications and effects (e.g., on angina, heart failure, or diabetic kidney disease). These considerations may guide selection of therapy. Exforge (amlodipine and valsartan) is indicated for the treatment of hypertension.

Exforge may be used in patients whose blood pressure is not adequately controlled on either monotherapy.

Exforge may also be used as initial therapy in patients who are likely to need multiple drugs to achieve their blood pressure goals.

The choice of Exforge as initial therapy for hypertension should be based on an assessment of potential benefits and risks including whether the patient is likely to tolerate the lowest dose of Exforge.

Patients with stage 2 hypertension (moderate or severe) are at a relatively higher risk for cardiovascular events (such as strokes, heart attacks, and heart failure), kidney failure and vision problems, so prompt treatment is clinically relevant. The decision to use a combination as initial therapy should be individualized and should be shaped by considerations such as baseline blood pressure, the target goal and the incremental likelihood of achieving goal with a combination compared to monotherapy. Individual blood pressure goals may vary based upon the patient’s risk.

Data from the high-dose multifactorial study [see Clinical Studies (14)] provide estimates of the probability of reaching a blood pressure goal with Exforge compared to amlodipine or valsartan monotherapy. The figures below provide estimates of the likelihood of achieving systolic or diastolic blood pressure control with Exforge 10/320 mg, based upon baseline systolic or diastolic blood pressure. The curve of each treatment group was estimated by logistic regression modeling. The estimated likelihood at the right tail of each curve is less reliable due to small numbers of subjects with high baseline blood pressures.

Figure 1: Probability of Achieving Systolic Blood Pressure <140 mmHg at Week 8 | Figure 2: Probability of Achieving Diastolic Blood Pressure <90 mmHg at Week 8
Figure 3: Probability of Achieving Systolic Blood Pressure <130 mmHg at Week 8 | Figure 4: Probability of Achieving Diastolic Blood Pressure <80 mmHg at Week 8

For example, a patient with a baseline blood pressure of 160/100 mmHg has about a 67% likelihood of achieving a goal of < 140 mmHg (systolic) and 80% likelihood of achieving < 90 mmHg (diastolic) on amlodipine alone, and the likelihood of achieving these goals on valsartan alone is about 47% (systolic) or 62% (diastolic). The likelihood of achieving these goals on Exforge rises to about 80% (systolic) or 85% (diastolic). The likelihood of achieving these goals on placebo is about 28% (systolic) or 37% (diastolic).

2 DOSAGE AND ADMINISTRATION

2.1 General Considerations

Dose once daily. The dosage can be increased after 1 to 2 weeks of therapy to a maximum of one 10/320 mg tablet once daily as needed to control blood pressure. The majority of the antihypertensive effect is attained within 2 weeks after initiation of therapy or a change in dose.

Exforge may be administered with other antihypertensive agents.

2.2 Add-on Therapy

A patient whose blood pressure is not adequately controlled with amlodipine (or another dihydropyridine calcium-channel blocker) alone or with valsartan (or another ARB) alone may be switched to combination therapy with Exforge.

A patient who experiences dose-limiting adverse reactions on either component alone may be switched to Exforge containing a lower dose of that component in combination with the other to achieve similar blood pressure reductions. The clinical response to Exforge should be subsequently evaluated and if blood pressure remains uncontrolled after 3 to 4 weeks of therapy, the dose may be titrated up to a maximum of 10/320 mg.

2.3 Replacement Therapy

For convenience, patients receiving amlodipine and valsartan from separate tablets may instead wish to receive tablets of Exforge containing the same component doses.

2.4 Initial Therapy

A patient may be initiated on Exforge if it is unlikely that control of blood pressure would be achieved with a single agent. The usual starting dose is Exforge 5/160 mg once daily in patients who are not volume-depleted.

3 DOSAGE FORMS AND STRENGTHS

Exforge (amlodipine and valsartan) tablets are available as follows:

5/160 mg tablets, debossed with NVR/ECE (side 1/side 2)

10/160 mg tablets, debossed with NVR/UIC

5/320 mg tablets, debossed with NVR/CSF

10/320 mg tablets, debossed with NVR/LUF

4 CONTRAINDICATIONS

Do not use in patients with known hypersensitivity to any component.

Do not coadminister aliskiren with Exforge in patients with diabetes [see Drug Interactions (7)].

5 WARNINGS AND PRECAUTIONS

5.1 Fetal Toxicity

Exforge can cause fetal harm when administered to a pregnant woman. Use of drugs that act on the renin-angiotensin system during the second and third trimesters of pregnancy reduces fetal renal function and increases fetal and neonatal morbidity and death. Resulting oligohydramnios can be associated with fetal lung hypoplasia and skeletal deformations. Potential neonatal adverse effects include skull hypoplasia, anuria, hypotension, renal failure, and death. When pregnancy is detected, discontinue Exforge as soon as possible [see Use in Specific Populations (8.1)].

5.2 Hypotension

Excessive hypotension was seen in 0.4% of patients with uncomplicated hypertension treated with Exforge in placebo-controlled studies. In patients with an activated renin-angiotensin system, such as volume- and/or salt-depleted patients receiving high doses of diuretics, symptomatic hypotension may occur in patients receiving angiotensin receptor blockers. Volume depletion should be corrected prior to administration of Exforge. Treatment with Exforge should start under close medical supervision.

Initiate therapy cautiously in patients with heart failure or recent myocardial infarction and in patients undergoing surgery or dialysis. Patients with heart failure or post-myocardial infarction patients given valsartan commonly have some reduction in blood pressure, but discontinuation of therapy because of continuing symptomatic hypotension usually is not necessary when dosing instructions are followed. In controlled trials in heart failure patients, the incidence of hypotension in valsartan-treated patients was 5.5% compared to 1.8% in placebo-treated patients. In the Valsartan in Acute Myocardial Infarction Trial (VALIANT), hypotension in post-myocardial infarction patients led to permanent discontinuation of therapy in 1.4% of valsartan-treated patients and 0.8% of captopril-treated patients.

Since the vasodilation induced by amlodipine is gradual in onset, acute hypotension has rarely been reported after oral administration. Nonetheless, caution, as with any other peripheral vasodilator, should be exercised when administering amlodipine, particularly in patients with severe aortic stenosis.

If excessive hypotension occurs with Exforge, place the patient in a supine position and, if necessary, give intravenous normal saline. A transient hypotensive response is not a contraindication to further treatment, which usually can be continued without difficulty once the blood pressure has stabilized.

5.3 Risk of Myocardial Infarction or Increased Angina

Worsening angina and acute myocardial infarction can develop after starting or increasing the dose of amlodipine, particularly in patients with severe obstructive coronary artery disease.

5.4 Impaired Renal Function

Changes in renal function including acute renal failure can be caused by drugs that inhibit the renin-angiotensin system and by diuretics. Patients whose renal function may depend in part on the activity of the renin-angiotensin system (e.g., patients with renal artery stenosis, chronic kidney disease, severe congestive heart failure, or volume depletion) may be at particular risk of developing acute renal failure on Exforge. Monitor renal function periodically in these patients. Consider withholding or discontinuing therapy in patients who develop a clinically significant decrease in renal function on Exforge [see Drug Interactions (7)].

5.5 Hyperkalemia

Drugs that inhibit the renin-angiotensin system can cause hyperkalemia. Monitor serum electrolytes periodically.

Some patients with heart failure have developed increases in potassium with valsartan therapy. These effects are usually minor and transient, and they are more likely to occur in patients with pre-existing renal impairment. Dosage reduction and/or discontinuation of Exforge may be required [see Adverse Reactions (6.1)].

6 ADVERSE REACTIONS

6.1 Clinical Trials Experience

Because clinical trials are conducted under widely varying conditions, adverse reaction rates observed in the clinical trials of a drug cannot be directly compared to rates in the clinical trials of another drug and may not reflect the rates observed in practice. The adverse reaction information from clinical trials does, however, provide a basis for identifying the adverse events that appear to be related to drug use and for approximating rates.

Studies with Exforge:

Exforge has been evaluated for safety in over 2600 patients with hypertension; over 1440 of these patients were treated for at least 6 months and over 540 of these patients were treated for at least 1 year. Adverse reactions have generally been mild and transient in nature and have only infrequently required discontinuation of therapy.

The hazards [see Warnings and Precautions (5)] of valsartan are generally independent of dose; those of amlodipine are a mixture of dose-dependent phenomena (primarily peripheral edema) and dose-independent phenomena, the former much more common than the latter.

The overall frequency of adverse reactions was neither dose-related nor related to gender, age, or race. In placebo-controlled clinical trials, discontinuation due to side effects occurred in 1.8% of patients in the Exforge-treated patients and 2.1% in the placebo-treated group. The most common reasons for discontinuation of therapy with Exforge were peripheral edema (0.4%), and vertigo (0.2%).

The adverse reactions that occurred in placebo-controlled clinical trials in at least 2% of patients treated with Exforge but at a higher incidence in amlodipine/valsartan patients (n=1437) than placebo (n=337) included peripheral edema (5.4% vs 3.0%), nasopharyngitis (4.3% vs 1.8%), upper respiratory tract infection (2.9% vs 2.1%) and dizziness (2.1% vs 0.9%).

Orthostatic events (orthostatic hypotension and postural dizziness) were seen in less than 1% of patients.

Studies with Valsartan:

Diovan® has been evaluated for safety in more than 4000 hypertensive patients in clinical trials. In trials in which valsartan was compared to an angiotensin-converting enzyme (ACE) inhibitor with or without placebo, the incidence of dry cough was significantly greater in the ACE inhibitor group (7.9%) than in the groups who received valsartan (2.6%) or placebo (1.5%). In a 129-patient trial limited to patients who had had dry cough when they had previously received ACE inhibitors, the incidences of cough in patients who received valsartan, HCTZ, or lisinopril were 20%, 19%, and 69% respectively (p<0.001).

Clinical Lab Test Findings:

Creatinine: In heart failure patients, greater than 50% increases in creatinine were observed in 3.9% of valsartan-treated patients compared to 0.9% of placebo-treated patients. In post-myocardial infarction patients, doubling of serum creatinine was observed in 4.2% of valsartan-treated patients and 3.4% of captopril-treated patients.

Blood Urea Nitrogen (BUN): In hypertensive patients, greater than 50% increases in BUN were observed in 5.5% of Exforge-treated patients compared to 4.7% of placebo-treated patients. In heart failure patients, greater than 50% increases in BUN were observed in 16.6% of valsartan-treated patients compared to 6.3% of placebo-treated patients [see Warnings and Precautions (5.4)].

Neutropenia: Neutropenia was observed in 1.9% of patients treated with Diovan and 0.8% of patients treated with placebo.

6.2 Postmarketing Experience

The following additional adverse reactions have been reported in postmarketing experience. Because these reactions are reported voluntarily from a population of uncertain size, it is not always possible to reliably estimate their frequency or establish a causal relationship to drug exposure.

Amlodipine: Gynecomastia has been reported infrequently and a causal relationship is uncertain. Jaundice and hepatic enzyme elevations (mostly consistent with cholestasis or hepatitis), in some cases severe enough to require hospitalization, have been reported in association with use of amlodipine.

Valsartan: The following additional adverse reactions have been reported in postmarketing experience with valsartan:

Hypersensitivity: Angioedema has been reported. Some of these patients previously experienced angioedema with other drugs including ACE inhibitors. Diovan should not be re-administered to patients who have had angioedema.

Digestive: Elevated liver enzymes and reports of hepatitis

Musculoskeletal: Rhabdomyolysis

Renal: Impaired renal function, renal failure

Dermatologic: Alopecia, bullous dermatitis

Blood and Lymphatic: Thrombocytopenia

Vascular: Vasculitis

7 DRUG INTERACTIONS

No drug interaction studies have been conducted with Exforge and other drugs, although studies have been conducted with the individual amlodipine and valsartan components.

Amlodipine

Impact of Other Drugs on Amlodipine

CYP3A Inhibitors

Coadministration with CYP3A inhibitors (moderate and strong) results in increased systemic exposure to amlodipine and may require dose reduction. Monitor for symptoms of hypotension and edema when amlodipine is coadministered with CYP3A inhibitors to determine the need for dose adjustment [see Clinical Pharmacology (12.3)].

CYP3A Inducers

No information is available on the quantitative effects of CYP3A inducers on amlodipine. Blood pressure should be closely monitored when amlodipine is coadministered with CYP3A inducers (e.g. rifampicin, St. John's Wort).

Sildenafil

Monitor for hypotension when sildenafil is coadministered with amlodipine [see Clinical Pharmacology (12.2)].

Impact of Amlodipine on Other Drugs

Simvastatin

Coadministration of simvastatin with amlodipine increases the systemic exposure of simvastatin. Limit the dose of simvastatin in patients on amlodipine to 20 mg daily [see Clinical Pharmacology (12.3)].

Immunosuppressants

Amlodipine may increase the systemic exposure of cyclosporine or tacrolimus when coadministered. Frequent monitoring of trough blood levels of cyclosporine and tacrolimus is recommended and adjust the dose when appropriate [see Clinical Pharmacology (12.3)].

Valsartan

Agents Increasing Serum Potassium: Concomitant use of valsartan with other agents that block the renin-angiotensin system, potassium-sparing diuretics (e.g., spironolactone, triamterene, amiloride), potassium supplements, salt substitutes containing potassium or other drugs that may increase potassium levels (e.g., heparin) may lead to increases in serum potassium and in heart failure patients to increases in serum creatinine. If co-medication is considered necessary, monitoring of serum potassium is advisable.

Non-Steroidal Anti-Inflammatory Agents Including Selective Cyclooxygenase-2 Inhibitors (COX-2 Inhibitors): In patients who are elderly, volume-depleted (including those on diuretic therapy), or with compromised renal function, coadministration of NSAIDs, including selective COX-2 inhibitors, with angiotensin II receptor antagonists, including valsartan, may result in deterioration of renal function, including possible acute renal failure. These effects are usually reversible. Monitor renal function periodically in patients receiving valsartan and NSAID therapy.

The antihypertensive effect of angiotensin II receptor antagonists, including valsartan, may be attenuated by NSAIDs including selective COX-2 inhibitors.

Dual Blockade of the Renin-Angiotensin System (RAS): Dual blockade of the RAS with angiotensin receptor blockers, ACE inhibitors, or aliskiren is associated with increased risks of hypotension, hyperkalemia, and changes in renal function (including acute renal failure) compared to monotherapy. Most patients receiving the combination of two RAS inhibitors do not obtain any additional benefit compared to monotherapy. In general, avoid combined use of RAS inhibitors. Closely monitor blood pressure, renal function and electrolytes in patients on valsartan and other agents that affect the RAS.

Do not coadminister aliskiren with Exforge in patients with diabetes. Avoid use of aliskiren with Exforge in patients with renal impairment (GFR <60 mL/min).

Lithium: Increases in serum lithium concentrations and lithium toxicity have been reported during concomitant administration of lithium with angiotensin II receptor antagonists. Monitor serum lithium levels during concomitant use.

8 USE IN SPECIFIC POPULATIONS

8.1 Pregnancy

Risk Summary

Exforge can cause fetal harm when administered to a pregnant woman. Use of drugs that act on the renin-angiotensin system during the second and third trimesters of pregnancy reduces fetal renal function and increases fetal and neonatal morbidity and death. Most epidemiologic studies examining fetal abnormalities after exposure to antihypertensive use in the first trimester have not distinguished drugs affecting the renin-angiotensin system from other antihypertensive agents. Published reports include cases of anhydramnios and oligohydramnios in pregnant women treated with valsartan (see Clinical Considerations).

When pregnancy is detected, discontinue EXFORGE as soon as possible.

The estimated background risk of major birth defects and miscarriage for the indicated population is unknown. All pregnancies have a background risk of birth defect, loss, or other adverse outcomes. In the U.S. general population, the estimated background risk of major birth defects and miscarriage in clinically recognized pregnancies is 2-4% and 15-20%, respectively.

Clinical Considerations

Disease-Associated Maternal and/or Embryo/Fetal risk

Hypertension in pregnancy increases the maternal risk for pre-eclampsia, gestational diabetes, premature delivery, and delivery complications (e.g., need for cesarean section, and post-partum hemorrhage). Hypertension increases the fetal risk for intrauterine growth restriction and intrauterine death. Pregnant women with hypertension should be carefully monitored and managed accordingly.

Fetal/Neonatal Adverse Reactions

Oligohydramnios in pregnant women who use drugs affecting the renin-angiotensin system in the second and third trimesters of pregnancy can result in the following: reduced fetal renal function leading to anuria and renal failure, fetal lung hypoplasia, skeletal deformations, including skull hypoplasia, hypotension and death.

Perform serial ultrasound examinations to assess the intra-amniotic environment. Fetal testing may be appropriate, based on the week of gestation. Patients and physicians should be aware, however, that oligohydramnios may not appear until after the fetus has sustained irreversible injury. If oligohydramnios is observed, consider alternative drug treatment. Closely observe neonates with histories of in utero exposure to Exforge for hypotension, oliguria, and hyperkalemia. In neonates with a history of in utero exposure to Exforge, if oliguria or hypotension occurs, support blood pressure and renal perfusion. Exchange transfusions or dialysis may be required as a means of reversing hypotension and replacing renal function.

Data

Animal Data

In rats, administered 20 mg/kg/day amlodipine plus 320 mg/kg/day valsartan, treatment-related maternal and fetal effects (developmental delays and alterations noted in the presence of significant maternal toxicity) were noted with the high dose combination. This corresponds to dose multiples of 9 and 19.5 times, respectively, the maximum recommended human dose (MRHD) of 10 mg/day for amlodipine and 320 mg/day for valsartan (based on body surface area and considering a 60 kg patient).

8.2 Lactation

Risk Summary

There is limited information regarding the presence of Exforge in human milk, the effects on the breastfed infant, or the effects on milk production. Valsartan is present in rat milk. Limited published studies report that amlodipine is present in human milk. Because of the potential for serious adverse reactions in breastfed infants, advise a nursing woman that breastfeeding is not recommended during treatment with Exforge.

Data

Valsartan was detected in the milk of lactating rats 15 minutes after oral administration of a 3 mg/kg dose.

8.4 Pediatric Use

Safety and effectiveness of Exforge in pediatric patients have not been established.

8.5 Geriatric Use

In controlled clinical trials, 323 (22.5%) hypertensive patients treated with Exforge were ≥ 65 years and 79 (5.5%) were ≥ 75 years. No overall differences in the efficacy or safety of Exforge was observed in this patient population, but greater sensitivity of some older individuals cannot be ruled out.

Amlodipine: The recommended starting dose of amlodipine 2.5 mg is not an available strength with Exforge.

Clinical studies of amlodipine besylate tablets did not include sufficient numbers of subjects aged 65 and over to determine whether they respond differently from younger subjects. Other reported clinical experience has not identified differences in responses between the elderly and younger patients. In general, dose selection for an elderly patient should be cautious, usually starting at the low end of the dosing range, reflecting the greater frequency of decreased hepatic, renal or cardiac function, and of concomitant disease or other drug therapy. Elderly patients have decreased clearance of amlodipine with a resulting increase of area under the curve (AUC) of approximately 40% to 60%.

Valsartan: In the controlled clinical trials of valsartan, 1214 (36.2%) of hypertensive patients treated with valsartan were ≥ 65 years and 265 (7.9%) were ≥ 75 years. No overall difference in the efficacy or safety of valsartan was observed in this patient population, but greater sensitivity of some older individuals cannot be ruled out.

8.6 Renal Impairment

Safety and effectiveness of Exforge in patients with severe renal impairment (CrCl < 30 mL/min) have not been established. No dose adjustment is required in patients with mild (CrCl 60 to 90 mL/min) or moderate (CrCl 30 to 60 mL/min) renal impairment.

8.7 Hepatic Impairment

Amlodipine

Exposure to amlodipine is increased in patients with hepatic insufficiency [see Clinical Pharmacology (12.3)]. The recommended initial dose of amlodipine in patients with hepatic impairment is 2.5 mg, which is not an available strength with Exforge.

Valsartan

No dose adjustment is necessary for patients with mild-to-moderate disease. No dosing recommendations can be provided for patients with severe liver disease.

10 OVERDOSAGE

Amlodipine

Single oral doses of amlodipine maleate equivalent to 40 mg/kg and 100 mg/kg amlodipine in mice and rats, respectively, caused deaths. Single oral doses equivalent to 4 or more mg/kg amlodipine in dogs (11 or more times the maximum recommended human dose on a mg/m^2 basis) caused a marked peripheral vasodilation and hypotension.

Overdosage might be expected to cause excessive peripheral vasodilation with marked hypotension. In humans, experience with intentional overdosage of amlodipine is limited. Marked and potentially prolonged systemic hypotension up to and including shock with fatal outcome have been reported.

If massive overdose should occur, initiate active cardiac and respiratory monitoring. Frequent blood pressure measurements are essential. Should hypotension occur, cardiovascular support including elevation of the extremities and the judicious administration of fluids should be initiated. If hypotension remains unresponsive to these conservative measures, consider administration of vasopressors (such as phenylephrine) with attention to circulating volume and urine output. As amlodipine is highly protein bound, hemodialysis is not likely to be of benefit. Administration of activated charcoal to healthy volunteers immediately or up to two hours after ingestion of amlodipine has been shown to significantly decrease amlodipine absorption.

Valsartan

Limited data are available related to overdosage in humans. The most likely effect of overdose with valsartan would be peripheral vasodilation, hypotension, and tachycardia; bradycardia could occur from parasympathetic (vagal) stimulation. Depressed level of consciousness, circulatory collapse, and shock have been reported. If symptomatic hypotension should occur, institute supportive treatment.

Valsartan is not removed from the plasma by hemodialysis.

Valsartan was without grossly observable adverse effects at single oral doses up to 2000 mg/kg in rats and up to 1000 mg/kg in marmosets, except for the salivation and diarrhea in the rat and vomiting in the marmoset at the highest dose (60 and 37 times, respectively, the MRHD on a mg/m^2 basis) (Calculations assume an oral dose of 320 mg/day and a 60 kg patient).

11 DESCRIPTION

Exforge is a fixed combination of amlodipine and valsartan.

Exforge contains the besylate salt of amlodipine, a dihydropyridine calcium-channel blocker (CCB). Amlodipine besylate is a white to pale yellow crystalline powder, slightly soluble in water and sparingly soluble in ethanol. Amlodipine besylate’s chemical name is 3-Ethyl-5-methyl(4RS)-2-[(2-aminoethoxy)methyl]-4-(2-chlorophenyl)-6-methyl-1,4-dihydropyridine-3,5-dicarboxylate benzenesulphonate; its structural formula is:

Its empirical formula is C20H25ClN2O5•C6H6O3S and its molecular weight is 567.1.

Valsartan is a nonpeptide, orally active, and specific angiotensin II antagonist acting on the AT1 receptor subtype. Valsartan is a white to practically white fine powder, soluble in ethanol and methanol and slightly soluble in water. Valsartan’s chemical name is N-(1-oxopentyl)-N-[[2’-(1H-tetrazol-5-yl) [1,1’-biphenyl]-4-yl]methyl]-L-valine; its structural formula is:

Its empirical formula is C24H29N5O3 and its molecular weight is 435.5.

Exforge tablets are formulated in 4 strengths for oral administration with a combination of amlodipine besylate (6.9 mg or 13.9 mg, equivalent to 5 mg or 10 mg of amlodipine respectively), with 160 mg, or 320 mg of valsartan providing for the following available combinations: 5/160 mg, 10/160 mg, 5/320 mg, and 10/320 mg.

The inactive ingredients for all strengths of the tablets are colloidal silicon dioxide, crospovidone, magnesium stearate, and microcrystalline cellulose. Additionally the 5/320 mg and 10/320 mg strengths contain iron oxide yellow and sodium starch glycolate. The film coating contains hypromellose, iron oxides, polyethylene glycol, talc, and titanium dioxide.

12 CLINICAL PHARMACOLOGY

12.1 Mechanism of Action

Amlodipine

Amlodipine is a dihydropyridine calcium channel blocker that inhibits the transmembrane influx of calcium ions into vascular smooth muscle and cardiac muscle. Experimental data suggest that amlodipine binds to both dihydropyridine and nondihydropyridine binding sites. The contractile processes of cardiac muscle and vascular smooth muscle are dependent upon the movement of extracellular calcium ions into these cells through specific ion channels. Amlodipine inhibits calcium ion influx across cell membranes selectively, with a greater effect on vascular smooth muscle cells than on cardiac muscle cells. Negative inotropic effects can be detected in vitro but such effects have not been seen in intact animals at therapeutic doses. Serum calcium concentration is not affected by amlodipine. Within the physiologic pH range, amlodipine is an ionized compound (pKa=8.6), and its kinetic interaction with the calcium channel receptor is characterized by a gradual rate of association and dissociation with the receptor binding site, resulting in a gradual onset of effect.

Amlodipine is a peripheral arterial vasodilator that acts directly on vascular smooth muscle to cause a reduction in peripheral vascular resistance and reduction in blood pressure.

Valsartan

Angiotensin II is formed from angiotensin I in a reaction catalyzed by angiotensin-converting enzyme (ACE, kininase II). Angiotensin II is the principal pressor agent of the renin-angiotensin system, with effects that include vasoconstriction, stimulation of synthesis and release of aldosterone, cardiac stimulation, and renal reabsorption of sodium. Valsartan blocks the vasoconstrictor and aldosterone-secreting effects of angiotensin II by selectively blocking the binding of angiotensin II to the AT1 receptor in many tissues, such as vascular smooth muscle and the adrenal gland. Its action is therefore independent of the pathways for angiotensin II synthesis.

There is also an AT2 receptor found in many tissues, but AT2 is not known to be associated with cardiovascular homeostasis. Valsartan has much greater affinity (about 20,000-fold) for the AT1 receptor than for the AT2 receptor. The increased plasma levels of angiotensin following AT1 receptor blockade with valsartan may stimulate the unblocked AT2 receptor. The primary metabolite of valsartan is essentially inactive with an affinity for the AT1 receptor about one-200th that of valsartan itself.

Blockade of the renin-angiotensin system with ACE inhibitors, which inhibit the biosynthesis of angiotensin II from angiotensin I, is widely used in the treatment of hypertension. ACE inhibitors also inhibit the degradation of bradykinin, a reaction also catalyzed by ACE. Because valsartan does not inhibit ACE (kininase II), it does not affect the response to bradykinin. Whether this difference has clinical relevance is not yet known. Valsartan does not bind to or block other hormone receptors or ion channels known to be important in cardiovascular regulation.

Blockade of the angiotensin II receptor inhibits the negative regulatory feedback of angiotensin II on renin secretion, but the resulting increased plasma renin activity and angiotensin II circulating levels do not overcome the effect of valsartan on blood pressure.

12.2 Pharmacodynamics

Amlodipine

Following administration of therapeutic doses to patients with hypertension, amlodipine produces vasodilation resulting in a reduction of supine and standing blood pressures. These decreases in blood pressure are not accompanied by a significant change in heart rate or plasma catecholamine levels with chronic dosing. Although the acute intravenous administration of amlodipine decreases arterial blood pressure and increases heart rate in hemodynamic studies of patients with chronic stable angina, chronic oral administration of amlodipine in clinical trials did not lead to clinically significant changes in heart rate or blood pressures in normotensive patients with angina.

With chronic, once-daily administration, antihypertensive effectiveness is maintained for at least 24 hours. Plasma concentrations correlate with effect in both young and elderly patients. The magnitude of reduction in blood pressure with amlodipine is also correlated with the height of pretreatment elevation; thus, individuals with moderate hypertension (diastolic pressure 105-114 mmHg) had about a 50% greater response than patients with mild hypertension (diastolic pressure 90-104 mmHg). Normotensive subjects experienced no clinically significant change in blood pressure (+1/-2 mmHg).

In hypertensive patients with normal renal function, therapeutic doses of amlodipine resulted in a decrease in renal vascular resistance and an increase in glomerular filtration rate and effective renal plasma flow without change in filtration fraction or proteinuria.

As with other calcium channel blockers, hemodynamic measurements of cardiac function at rest and during exercise (or pacing) in patients with normal ventricular function treated with amlodipine have generally demonstrated a small increase in cardiac index without significant influence on dP/dt or on left ventricular end diastolic pressure or volume. In hemodynamic studies, amlodipine has not been associated with a negative inotropic effect when administered in the therapeutic dose range to intact animals and man, even when coadministered with beta-blockers to man. Similar findings, however, have been observed in normal or well-compensated patients with heart failure with agents possessing significant negative inotropic effects.

Amlodipine does not change sinoatrial nodal function or atrioventricular (AV) conduction in intact animals or man. In patients with chronic stable angina, intravenous administration of 10 mg did not significantly alter A-H and H-V conduction and sinus node recovery time after pacing. Similar results were obtained in patients receiving amlodipine and concomitant beta-blockers. In clinical studies in which amlodipine was administered in combination with beta-blockers to patients with either hypertension or angina, no adverse effects of electrocardiographic (ECG) parameters were observed. In clinical trials with angina patients alone, amlodipine therapy did not alter electrocardiographic intervals or produce higher degrees of AV blocks.

Amlodipine has indications other than hypertension which can be found in the Norvasc* package insert.

Drug Interactions

Sildenafil

When amlodipine and sildenafil were used in combination, each agent independently exerted its own blood pressure lowering effect [see Drug Interactions (7)].

Valsartan

Valsartan inhibits the pressor effect of angiotensin II infusions. An oral dose of 80 mg inhibits the pressor effect by about 80% at peak with approximately 30% inhibition persisting for 24 hours. No information on the effect of larger doses is available.

Removal of the negative feedback of angiotensin II causes a 2- to 3-fold rise in plasma renin and consequent rise in angiotensin II plasma concentration in hypertensive patients. Minimal decreases in plasma aldosterone were observed after administration of valsartan; very little effect on serum potassium was observed.

In multiple dose studies in hypertensive patients with stable renal insufficiency and patients with renovascular hypertension, valsartan had no clinically significant effects on glomerular filtration rate, filtration fraction, creatinine clearance, or renal plasma flow.

Administration of valsartan to patients with essential hypertension results in a significant reduction of sitting, supine, and standing systolic blood pressure, usually with little or no orthostatic change. Valsartan has indications other than hypertension which can be found in the Diovan package insert.

Exforge

Exforge has been shown to be effective in lowering blood pressure. Both amlodipine and valsartan lower blood pressure by reducing peripheral resistance, but calcium influx blockade and reduction of angiotensin II vasoconstriction are complementary mechanisms.

12.3 Pharmacokinetics

Amlodipine

Peak plasma concentrations of amlodipine are reached 6 to 12 hours after administration of amlodipine alone. Absolute bioavailability has been estimated to be between 64% and 90%. The bioavailability of amlodipine is not altered by the presence of food.

The apparent volume of distribution of amlodipine is 21 L/kg. Approximately 93% of circulating amlodipine is bound to plasma proteins in hypertensive patients.

Amlodipine is extensively (about 90%) converted to inactive metabolites via hepatic metabolism with 10% of the parent compound and 60% of the metabolites excreted in the urine.

Elimination of amlodipine from the plasma is biphasic with a terminal elimination half-life of about 30 to 50 hours. Steady state plasma levels of amlodipine are reached after 7 to 8 days of consecutive daily dosing.

Valsartan

Following oral administration of valsartan alone peak plasma concentrations of valsartan are reached in 2 to 4 hours. Absolute bioavailability is about 25% (range 10% to 35%). Food decreases the exposure (as measured by AUC) to valsartan by about 40% and peak plasma concentration (Cmax) by about 50%.

The steady state volume of distribution of valsartan after intravenous administration is 17 L, indicating that valsartan does not distribute into tissues extensively. Valsartan is highly bound to serum proteins (95%), mainly serum albumin.

Valsartan shows biexponential decay kinetics following intravenous administration with an average elimination half-life of about 6 hours. The recovery is mainly as unchanged drug, with only about 20% of dose recovered as metabolites. The primary metabolite, accounting for about 9% of dose, is valeryl 4-hydroxy valsartan. In vitro metabolism studies involving recombinant CYP 450 enzymes indicated that the CYP 2C9 isoenzyme is responsible for the formation of valeryl-4-hydroxy valsartan. Valsartan does not inhibit CYP 450 isozymes at clinically relevant concentrations. CYP 450 mediated drug interaction between valsartan and coadministered drugs are unlikely because of the low extent of metabolism.

Valsartan, when administered as an oral solution, is primarily recovered in feces (about 83% of dose) and urine (about 13% of dose). Following intravenous administration, plasma clearance of valsartan is about 2 L/h and its renal clearance is 0.62 L/h (about 30% of total clearance).

Exforge

Following oral administration of Exforge in normal healthy adults, peak plasma concentrations of valsartan and amlodipine are reached in 3 and 6 to 8 hours, respectively. The rate and extent of absorption of valsartan and amlodipine from Exforge are the same as when administered as individual tablets. The bioavailabilities of amlodipine and valsartan are not altered by the coadministration of food. Exforge may be administered with or without food.

Specific Populations

Geriatric

Amlodipine: Elderly patients have decreased clearance of amlodipine with a resulting increase in peak plasma levels, elimination half-life and AUC.

Valsartan: Exposure (measured by AUC) to valsartan is higher by 70% and the half-life is longer by 35% in the elderly than in the young. No dosage adjustment is necessary.

Gender

Valsartan: Pharmacokinetics of valsartan does not differ significantly between males and females.

Renal Insufficiency

Amlodipine: The pharmacokinetics of amlodipine is not significantly influenced by renal impairment.

Valsartan: There is no apparent correlation between renal function (measured by creatinine clearance) and exposure (measured by AUC) to valsartan in patients with different degrees of renal impairment. Consequently, dose adjustment is not required in patients with mild-to-moderate renal dysfunction. No studies have been performed in patients with severe impairment of renal function (creatinine clearance <10 mL/min). Valsartan is not removed from the plasma by hemodialysis. In the case of severe renal disease, exercise care with dosing of valsartan.

Hepatic Insufficiency

Amlodipine: Patients with hepatic insufficiency have decreased clearance of amlodipine with resulting increase in AUC of approximately 40% to 60%.

Valsartan: On average, patients with mild-to-moderate chronic liver disease have twice the exposure (measured by AUC values) to valsartan of healthy volunteers (matched by age, sex and weight). In general, no dosage adjustment is needed in patients with mild-to-moderate liver disease. Care should be exercised in patients with liver disease.

Drug Interactions

Amlodipine

In vitro data in human plasma indicate that amlodipine has no effect on the protein binding of digoxin, phenytoin, warfarin and indomethacin.

Impact of Other Drugs on Amlodipine

Coadministered cimetidine, magnesium-and aluminum hydroxide antacids, sildenafil, and grapefruit juice have no impact on the exposure to amlodipine.

CYP3A Inhibitors: Co-administration of a 180 mg daily dose of diltiazem with 5 mg amlodipine in elderly hypertensive patients resulted in a 60% increase in amlodipine systemic exposure. Erythromycin co-administration in healthy volunteers did not significantly change amlodipine systemic exposure. However, strong inhibitors of CYP3A (e.g., itraconazole, clarithromycin) may increase the plasma concentrations of amlodipine to a greater extent [see Drug Interactions (7)].

Impact of Amlodipine on Other Drugs

Coadministered amlodipine does not affect the exposure to atorvastatin, digoxin, ethanol and the warfarin prothrombin response time.

Simvastatin: Coadministration of multiple doses of 10 mg of amlodipine with 80 mg simvastatin resulted in a 77% increase in exposure to simvastatin compared to simvastatin alone [see Drug Interactions (7)].

Cyclosporine: A prospective study in renal transplant patients (N=11) showed an average of 40% increase in trough cyclosporine levels when concomitantly treated with amlodipine [see Drug Interactions (7)].

Tacrolimus: A prospective study in healthy Chinese volunteers (N=9) with CYP3A5 expressers showed a 2.5-to 4-fold increase in tacrolimus exposure when concomitantly administered with amlodipine compared to tacrolimus alone. This finding was not observed in CYP3A5 non-expressers (N=6). However, a 3-fold increase in plasma exposure to tacrolimus in a renal transplant patient (CYP3A5 non-expresser) upon initiation of amlodipine for the treatment of post-transplant hypertension resulting in reduction of tacrolimus dose has been reported. Irrespective of the CYP3A5 genotype status, the possibility of an interaction cannot be excluded with these drugs [see Drug Interactions (7)].

Valsartan

No clinically significant pharmacokinetic interactions were observed when valsartan was coadministered with amlodipine, atenolol, cimetidine, digoxin, furosemide, glyburide, hydrochlorothiazide, or indomethacin. The valsartan-atenolol combination was more antihypertensive than either component, but it did not lower the heart rate more than atenolol alone.

Coadministration of valsartan and warfarin did not change the pharmacokinetics of valsartan or the time-course of the anticoagulant properties of warfarin.

Transporters: The results from an in vitro study with human liver tissue indicate that valsartan is a substrate of the hepatic uptake transporter OATP1B1 and the hepatic efflux transporter MRP2. Coadministration of inhibitors of the uptake transporter (rifampin, cyclosporine) or efflux transporter (ritonavir) may increase the systemic exposure to valsartan.

13 NONCLINICAL TOXICOLOGY

13.1 Carcinogenesis, Mutagenesis, Impairment of Fertility

Amlodipine

Rats and mice treated with amlodipine maleate in the diet for up to 2 years, at concentrations calculated to provide daily dosage levels of 0.5, 1.25, and 2.5 mg amlodipine/kg/day, showed no evidence of a carcinogenic effect of the drug. For the mouse, the highest dose was, on mg/m^2 basis, similar to the MRHD of 10 mg amlodipine/day. For the rat, the highest dose was, on a mg/m^2 basis, about 2.5 the MRHD (Calculations based on a 60 kg patient).

Mutagenicity studies conducted with amlodipine maleate revealed no drug-related effects at either the gene or chromosome level.

There was no effect on the fertility of rats treated orally with amlodipine maleate (males for 64 days and females for 14 days prior to mating) at doses of up to 10 mg amlodipine/kg/day (about 10 times the MRHD of 10 mg/day on a mg/m^2 basis).

Valsartan

There was no evidence of carcinogenicity when valsartan was administered in the diet to mice and rats for up to 2 years at concentrations calculated to provide doses of up to 160 and 200 mg/kg/day, respectively. These doses in mice and rats are about 2.4 and 6 times, respectively, the MRHD of 320 mg/day on a mg/m^2 basis. (Calculations based on a 60 kg patient.)

Mutagenicity assays did not reveal any valsartan-related effects at either the gene or chromosome level. These assays included bacterial mutagenicity tests with Salmonella and E. coli, a gene mutation test with Chinese hamster V79 cells, a cytogenetic test with Chinese hamster ovary cells, and a rat micronucleus test.

Valsartan had no adverse effects on the reproductive performance of male or female rats at oral doses of up to 200 mg/kg/day. This dose is about 6 times the MRHD on a mg/m^2 basis.

14 CLINICAL STUDIES

Exforge was studied in 2 placebo-controlled and 4 active-controlled trials in hypertensive patients. In a double-blind, placebo-controlled study, a total of 1012 patients with mild-to-moderate hypertension received treatments of 3 combinations of amlodipine and valsartan (5/80, 5/160, 5/320 mg) or amlodipine alone (5 mg), valsartan alone (80, 160, or 320 mg) or placebo. All doses with the exception of the 5/320 mg dose were initiated at the randomized dose. The high dose was titrated to that dose after a week at a dose of 5/160 mg. At week 8, the combination treatments were statistically significantly superior to their monotherapy components in reduction of diastolic and systolic blood pressures.

Table 1: Effect of Exforge on Sitting Diastolic Blood Pressure
Amlodipine dosage | Valsartan dosage
 | 0 mg |  | 80 mg |  | 160 mg |  | 320 mg
 | Mean Change* | Placebo-subtracted | Mean Change* | Placebo-subtracted | Mean Change* | Placebo-subtracted | Mean Change* | Placebo-subtracted
0 mg | -6.4 | --- | -9.5 | -3.1 | -10.9 | -4.5 | -13.2 | -6.7
5 mg | -11.1 | -4.7 | -14.2 | -7.8 | -14.0 | -7.6 | -15.7 | -9.3
*Mean Change and Placebo-Subtracted Mean Change from Baseline (mmHg) at Week 8 in Sitting Diastolic Blood Pressure. Mean baseline diastolic BP was 99.3 mmHg.

Table 2: Effect of Exforge on Sitting Systolic Blood Pressure
Amlodipine dosage | Valsartan dosage
 | 0 mg |  | 80 mg |  | 160 mg |  | 320 mg
 | Mean Change* | Placebo-subtracted | Mean Change* | Placebo-subtracted | Mean Change* | Placebo-subtracted | Mean Change* | Placebo-subtracted
0 mg | -6.2 | --- | -12.9 | -6.8 | -14.3 | -8.2 | -16.3 | -10.1
5 mg | -14.8 | -8.6 | -20.7 | -14.5 | -19.4 | -13.2 | -22.4 | -16.2
*Mean Change and Placebo-Subtracted Mean Change from Baseline (mmHg) at Week 8 in Sitting Systolic Blood Pressure. Mean baseline systolic BP was 152.8 mmHg.

In a double-blind, placebo-controlled study, a total of 1246 patients with mild to moderate hypertension received treatments of 2 combinations of amlodipine and valsartan (10/160, 10/320 mg), or amlodipine alone (10 mg), valsartan alone (160 or 320 mg) or placebo. With the exception of the 10/320 mg dose, treatment was initiated at the randomized dose. The high dose was initiated at a dose of 5/160 mg and titrated to the randomized dose after 1 week. At week 8, the combination treatments were statistically significantly superior to their monotherapy components in reduction of diastolic and systolic blood pressures.

Table 3: Effect of Exforge on Sitting Diastolic Blood Pressure
Amlodipine dosage | Valsartan dosage
 | 0 mg |  | 160 mg |  | 320 mg
 | Mean Change* | Placebo-subtracted | Mean Change* | Placebo-subtracted | Mean Change* | Placebo-subtracted
0 mg | -8.2 | --- | -12.8 | - 4.5 | -12.8 | -4.5
10 mg | -15.0 | -6.7 | -17.2 | -9.0 | -18.1 | -9.9
*Mean Change and Placebo-Subtracted Mean Change from Baseline (mmHg) at Week 8 in Sitting Diastolic Blood Pressure. Mean baseline diastolic BP was 99.1 mmHg.

Table 4: Effect of Exforge on Sitting Systolic Blood Pressure
Amlodipine dosage | Valsartan dosage
 | 0 mg |  | 160 mg |  | 320 mg
 | Mean Change* | Placebo-subtracted | Mean Change* | Placebo-subtracted | Mean Change* | Placebo-subtracted
0 mg | -11.0 | --- | -18.1 | -7.0 | -18.5 | -7.5
10 mg | -22.2 | -11.2 | -26.6 | -15.5 | -26.9 | -15.9
*Mean Change and Placebo-Subtracted Mean Change from Baseline (mmHg) at Week 8 in Sitting Systolic Blood Pressure. Mean baseline systolic BP was 156.7 mmHg.

In a double-blind, active-controlled study, a total of 947 patients with mild to moderate hypertension who were not adequately controlled on valsartan 160 mg received treatments of 2 combinations of amlodipine and valsartan (10/160, 5/160 mg) or valsartan alone (160 mg). At week 8, the combination treatments were statistically significantly superior to the monotherapy component in reduction of diastolic and systolic blood pressures.

Table 5: Effect of Exforge on Sitting Diastolic/Systolic Blood Pressure
Treatment Group | Diastolic BP |  | Systolic BP
 | Mean change* | Treatment Difference** | Mean change* | Treatment Difference**
Exforge 10/160 mg | -11.4 | -4.8 | -13.9 | -5.7
Exforge 5/160 mg | -9.6 | -3.1 | -12.0 | -3.9
Valsartan 160 mg | -6.6 | --- | -8.2 | ---
*Mean Change from Baseline at Week 8 in Sitting Diastolic/Systolic Blood Pressure. Mean baseline BP was 149.5/96.5 (systolic/diastolic) mmHg.
**Treatment Difference = difference in mean BP reduction between Exforge and the control group (Valsartan 160 mg).

In a double-blind, active-controlled study, a total of 944 patients with mild to moderate hypertension who were not adequately controlled on amlodipine 10 mg received a combination of amlodipine and valsartan (10/160 mg) or amlodipine alone (10 mg). At week 8, the combination treatment was statistically significantly superior to the monotherapy component in reduction of diastolic and systolic blood pressures.

Table 6: Effect of Exforge on Sitting Diastolic/Systolic Blood Pressure
Treatment Group | Diastolic BP |  | Systolic BP
 | Mean change* | Treatment Difference** | Mean change* | Treatment Difference**
Exforge 10/160 mg | -11.8 | -1.8 | -12.7 | -1.9
Amlodipine 10 mg | -10.0 | --- | -10.8 | ---
*Mean Change from Baseline at Week 8 in Sitting Diastolic/Systolic Blood Pressure. Mean baseline BP was 147.0/95.1 (systolic/diastolic) mmHg.
**Treatment Difference = difference in mean BP reduction between Exforge and the control group (Amlodipine 10 mg).

Exforge was also evaluated for safety in a 6-week, double-blind, active-controlled trial of 130 hypertensive patients with severe hypertension (mean baseline BP of 171/113 mmHg). Adverse events were similar in patients with severe hypertension and mild/moderate hypertension treated with Exforge.

A wide age range of the adult population, including the elderly was studied (range 19 to 92 years, mean 54.7 years). Women comprised almost half of the studied population (47.3%). Of the patients in the studied Exforge group, 87.6% were Caucasian. Black and Asian patients each represented approximately 4% of the population in the studied Exforge group.

Two additional double-blind, active-controlled studies were conducted in which Exforge was administered as initial therapy. In 1 study, a total of 572 black patients with moderate to severe hypertension were randomized to receive either combination amlodipine/valsartan or amlodipine monotherapy for 12 weeks. The initial dose of amlodipine/valsartan was 5/160 mg for 2 weeks with forced titration to 10/160 mg for 2 weeks, followed by optional titration to 10/320 mg for 4 weeks and optional addition of HCTZ 12.5 mg for 4 weeks. The initial dose of amlodipine was 5 mg for 2 weeks with forced titration to 10 mg for 2 weeks, followed by optional titration to 10 mg for 4 weeks and optional addition of HCTZ 12.5 mg for 4 weeks. At the primary endpoint of 8 weeks, the treatment difference between amlodipine/valsartan and amlodipine was 6.7/2.8 mmHg.

In the other study of similar design, a total of 646 patients with moderate to severe hypertension (MSSBP of ≥ 160 mmHg and < 200 mmHg) were randomized to receive either combination amlodipine/valsartan or amlodipine monotherapy for 8 weeks. The initial dose of amlodipine/valsartan was 5/160 mg for 2 weeks with forced titration to 10/160 mg for 2 weeks, followed by the optional addition of HCTZ 12.5 mg for 4 weeks. The initial dose of amlodipine was 5 mg for 2 weeks with forced titration to 10 mg for 2 weeks, followed by the optional addition of HCTZ 12.5 mg for 4 weeks. At the primary endpoint of 4 weeks, the treatment difference between amlodipine/valsartan and amlodipine was 6.6/3.9 mmHg.

There are no trials of the Exforge combination tablet demonstrating reductions in cardiovascular risk in patients with hypertension, but the amlodipine component and several ARBs, which are the same pharmacological class as the valsartan component, have demonstrated such benefits.

16 HOW SUPPLIED/STORAGE AND HANDLING

Exforge is available as non-scored tablets containing amlodipine besylate (6.9 mg or 13.9 mg, equivalent to 5 mg or 10 mg of amlodipine respectively) with valsartan 160 mg or 320 mg, providing for the following available combinations: 5/160 mg, 10/160 mg, 5/320 mg, and 10/320 mg.

All strengths are packaged in bottles of 30 tablets.

5/160 mg Tablets - dark yellow, ovaloid shaped, film-coated tablet with beveled edge, debossed with “NVR” on one side and “ECE” on the other side.

Bottles of 30 NDC 0078-0488-15

10/160 mg Tablets - light yellow, ovaloid shaped, film-coated tablet with beveled edge, debossed with “NVR” on one side and “UIC” on the other side.

Bottles of 30 NDC 0078-0489-15

5/320 mg Tablets - very dark yellow, ovaloid shaped, film-coated tablet with beveled edge, debossed with “NVR” on one side and “CSF” on the other side.

Bottles of 30 NDC 0078-0490-15

10/320 mg Tablets - dark yellow, ovaloid shaped, film-coated tablet with beveled edge, debossed with “NVR” on one side and “LUF” on the other side.

Bottles of 30 NDC 0078-0491-15

Store at 20°C-25°C (68°F-77°F); excursions permitted between 15°C and 30°C (59°F and 86°F) [See USP Controlled Room Temperature]. Protect from moisture.

17 PATIENT COUNSELING INFORMATION

Information for Patients

Advise the patient to read the FDA-approved patient labeling (Patient Information).

Pregnancy: Advise female patients of childbearing age about the consequences of exposure to Exforge during pregnancy. Discuss treatment options with women planning to become pregnant. Ask patients to report pregnancies to their physicians as soon as possible [see Warnings and Precautions (5.1), Use in Specific Populations (8.1)].

Lactation: Advise women not to breastfeed during treatment with Exforge [see Use in Specific Populations (8.2)].

Symptomatic Hypotension: Advise patients that lightheadedness can occur, especially during the first days of therapy, and that it should be reported to their healthcare provider. Tell patients that if syncope occurs to discontinue Exforge until the physician has been consulted. Caution all patients that inadequate fluid intake, excessive perspiration, diarrhea, or vomiting can lead to an excessive fall in blood pressure, with the same consequences of lightheadedness and possible syncope [see Warnings and Precautions (5.2)].

Hyperkalemia: Advise patients not to use salt substitutes without consulting their healthcare provider [see Drug Interactions (7)].

T2021-18

FDA-APPROVED PATIENT LABELING

PATIENT INFORMATION

EXFORGE® (X-phorj)

(amlodipine and valsartan) Tablets

Read the Patient Information that comes with EXFORGE before you start taking it and each time you get a refill. There may be new information. This leaflet does not take the place of talking with your doctor about your medical condition or treatment. If you have any questions about EXFORGE, ask your doctor or pharmacist.

What is the most important information I should know about EXFORGE?

- EXFORGE can cause harm or death to an unborn baby.
- Talk to your doctor about other ways to lower your blood pressure if you plan to become pregnant.
- If you get pregnant while taking EXFORGE, tell your doctor right away.

What is EXFORGE?

EXFORGE contains 2 prescription medicines:

1. amlodipine, a calcium channel blocker
2. valsartan, an angiotensin receptor blocker (ARB).

EXFORGE may be used to lower high blood pressure (hypertension) in adults

- when 1 medicine to lower your high blood pressure is not enough
- as the first medicine to lower high blood pressure if your doctor decides you are likely to need more than 1 medicine.

EXFORGE has not been studied in children under 18 years of age.

What should I tell my doctor before taking EXFORGE?

Tell your doctor about all of your medical conditions, including if you:

- are pregnant or plan to become pregnant. See “What is the most important information I should know about EXFORGE?”
- are breastfeeding or plan to breastfeed. EXFORGE is present in human milk. It is not known whether EXFORGE affects your breastfed baby or milk production. Do not breastfeed while you are taking EXFORGE.
- have heart problems
- have liver problems
- have kidney problems
- are vomiting or having a lot of diarrhea
- have ever had a reaction called angioedema to another blood pressure medicine. Angioedema causes swelling of the face, lips, tongue, throat, and may cause difficulty breathing.

Tell your doctor about all the medicines you take, including prescription and nonprescription medicines, vitamins, and herbal supplements. Some of your other medicines and EXFORGE could affect each other, causing serious side effects.

Especially tell your doctor if you take:

- simvastatin or other cholesterol-lowering medicine
- other medicines for high blood pressure or a heart problem
- water pills (diuretics)
- potassium supplements. Your doctor may check the amount of potassium in your blood periodically.
- a salt substitute. Your doctor may check the amount of potassium in your blood periodically.
- nonsteroidal anti-inflammatory drugs (like ibuprofen or naproxen)
- medicines used to prevent and treat fungal skin infections (such as ketoconazole, itraconazole)
- medicines used to treat bacterial infections (such as clarithromycin, telithromycin)
- certain antibiotics (rifamycin group), a drug used to protect against transplant rejection (cyclosporine) or an antiretroviral drug used to treat HIV/AIDS infection (ritonavir). These drugs may increase the effect of valsartan.
- lithium, a medicine used in some types of depression

Know the medicines you take. Keep a list of your medicines and show it to your doctor or pharmacist when you get a new medicine. Talk to your doctor or pharmacist before you start taking any new medicine. Your doctor or pharmacist will know what medicines are safe to take together.

How should I take EXFORGE?

- Take EXFORGE exactly as your doctor tells you.
- Take EXFORGE once each day.
- EXFORGE can be taken with or without food.
- If you miss a dose, take it as soon as you remember. If it is close to your next dose, do not take the missed dose. Just take the next dose at your regular time.
- If you take too much EXFORGE, call your doctor or Poison Control Center, or go to the emergency room.
- Tell all your doctors or dentist you are taking EXFORGE if you:
  - are going to have surgery
  - go for kidney dialysis

What should I avoid while taking EXFORGE?

You should not take EXFORGE during pregnancy. See “What is the most important information I should know about EXFORGE?”

What are the possible side effects of EXFORGE?

EXFORGE may cause serious side effects including:

- harm to an unborn baby causing injury and even death. See “What is the most important information I should know about EXFORGE?”
- low blood pressure (hypotension). Low blood pressure is most likely to happen if you:
  - take water pills
  - are on a low-salt diet
  - get dialysis treatments
  - have heart problems
  - get sick with vomiting or diarrhea
  - drink alcohol

Lie down if you feel faint or dizzy. Call your doctor right away.

- more heart attacks and chest pain (angina) in people that already have severe heart problems. This may happen when you start EXFORGE or when there is an increase in your dose of EXFORGE. Get emergency help if you get worse chest pain or chest pain that does not go away.
- kidney problems. Kidney problems may become worse in people that already have kidney disease. Some people will have changes in blood tests for kidney function and may need a lower dose of EXFORGE. Call your doctor if you have swelling in your feet, ankles, or hands or unexplained weight gain. If you have heart failure, your doctor should check your kidney function before prescribing EXFORGE.
- laboratory blood test changes in people with heart failure. Some people with heart failure who take valsartan, 1 of the medicines in EXFORGE, have changes in blood tests including increased potassium and decreased kidney function.

The most common side effects of EXFORGE include:

- swelling (edema) of the hands, ankles, or feet
- nasal congestion, sore throat, and discomfort when swallowing
- upper respiratory tract infection (head or chest cold)
- dizziness

Tell your doctor if you have any side effect that bothers you or that does not go away.

These are not all the possible side effects of EXFORGE. For more information, ask your doctor or pharmacist.

Call your doctor for medical advice about side effects. You may report side effects to FDA at 1-800-FDA-1088.

How should I store EXFORGE?

- Store EXFORGE at room temperature between 59°F and 86°F (15°C and 30°C).
- Keep EXFORGE dry (protect it from moisture).

Keep EXFORGE and all medicines out of the reach of children.

General Information about EXFORGE

Medicines are sometimes prescribed for conditions that are not mentioned in the patient information leaflet. Do not use EXFORGE for a condition for which it was not prescribed. Do not give EXFORGE to other people, even if they have the same symptoms that you have. It may harm them.

This patient information leaflet summarizes the most important information about EXFORGE. If you would like more information about EXFORGE, talk with your doctor. You can ask your doctor or pharmacist for information about EXFORGE that is written for health professionals. For more information, call 1-888-669-6682.

What are the ingredients in EXFORGE?

Active ingredients: Amlodipine besylate and valsartan

The inactive ingredients of all strengths of the tablets are colloidal silicon dioxide, crospovidone, magnesium stearate, and microcrystalline cellulose. Additionally, the 5/320 mg and 10/320 mg strengths contain iron oxide yellow and sodium starch glycolate. The film coating contains hypromellose, iron oxides, polyethylene glycol, talc, and titanium dioxide.

What is high blood pressure (hypertension)?

Blood pressure is the force of blood in your blood vessels when your heart beats and when your heart rests. You have high blood pressure when the force is too much. EXFORGE can help your blood vessels relax so your blood pressure is lower. Medicines that lower blood pressure lower your chance of having a stroke or heart attack.

High blood pressure makes the heart work harder to pump blood throughout the body and causes damage to blood vessels. If high blood pressure is not treated, it can lead to stroke, heart attack, heart failure, kidney failure, and vision problems.

*Norvasc® is a registered trademark of Pfizer, Inc.

Distributed by:
Novartis Pharmaceuticals Corporation
East Hanover, New Jersey 07936

©Novartis

T2024-82
Revised: December 2024

PRINCIPAL DISPLAY PANEL

NDC 0078-0488-15

EXFORGE®
(amlodipine and valsartan)
Tablets

5 mg*/160 mg

*each tablet contains 6.9 mg of amlodipine besylate

30 tablets

Rx only

NOVARTIS

PRINCIPAL DISPLAY PANEL

NDC 0078-0489-15

EXFORGE®
(amlodipine and valsartan)
Tablets

10 mg*/160 mg

*each tablet contains 13.9 mg of amlodipine besylate

30 tablets

Rx only

NOVARTIS

PRINCIPAL DISPLAY PANEL

NDC 0078-0490-15

EXFORGE®
(amlodipine and valsartan)
Tablets

5 mg*/320 mg

*each tablet contains 6.9 mg of amlodipine besylate

30 tablets

Rx only

NOVARTIS

PRINCIPAL DISPLAY PANEL

NDC 0078-0491-15

EXFORGE®
(amlodipine and valsartan)
Tablets

10 mg*/320 mg

*each tablet contains 13.9 mg of amlodipine besylate

30 tablets

Rx only

NOVARTIS